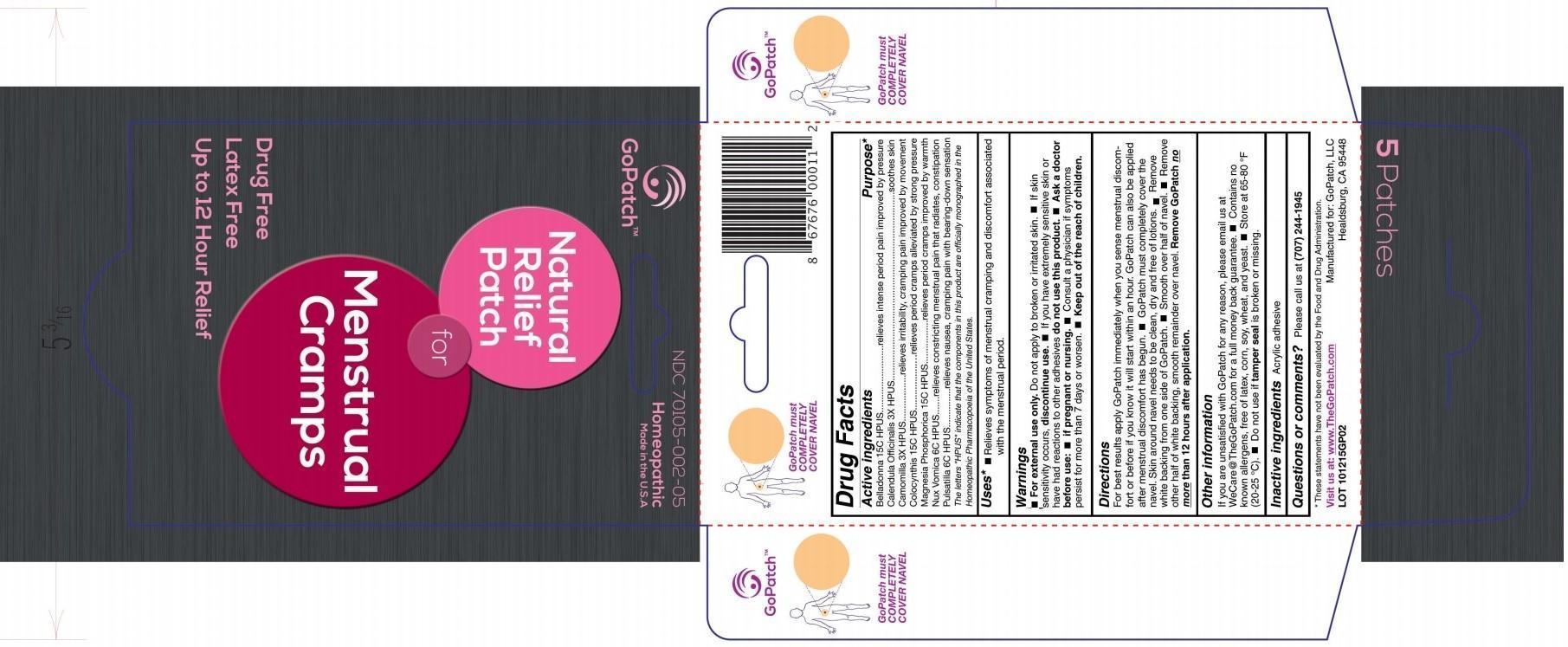 DRUG LABEL: Natural Relief Patch for MENSTRUAL CRAMPS
NDC: 70105-002 | Form: PATCH
Manufacturer: Centered Enterprises, LLC
Category: homeopathic | Type: HUMAN OTC DRUG LABEL
Date: 20240115

ACTIVE INGREDIENTS: PULSATILLA VULGARIS 6 [hp_C]/1 1; ATROPA BELLADONNA 15 [hp_C]/1 1; CALENDULA OFFICINALIS FLOWERING TOP 3 [hp_X]/1 1; MATRICARIA RECUTITA 3 [hp_X]/1 1; CITRULLUS COLOCYNTHIS FRUIT PULP 15 [hp_C]/1 1; MAGNESIUM PHOSPHATE, DIBASIC TRIHYDRATE 15 [hp_C]/1 1; STRYCHNOS NUX-VOMICA SEED 6 [hp_C]/1 1
INACTIVE INGREDIENTS: POLYVINYL ACETATE; WATER; ALCOHOL

MENSTRUAL CRAMPS

Active ingredients | Purpose*
Belladonna 15C HPUS | relieves intense period pain improved by pressure
Calendula Officinalis 3X HPUS | soothes skin
Chamomilla 3X HPUS | relieves irritability, cramping pain improved by movement
Colocynthis 15C HPUS | relieves period cramps alleviated by strong pressure
Magnesia Phosphorica 15C HPUS | relieves period cramps improved by warmth
Nux Vomica 6C HPUS | relieves constricting menstrual pain that radiates, constipation
Pulsatilla 6C HPUS | relieves nausea, cramping pain with bearing-down sensation

The letters "HPUS" indicate that the components in this product are officially monographed in the Homeopathic Pharmacopoeia of the United States.

Uses*

- Relieves symptoms of menstrual cramping and discomfort associated with the menstrual period.

Warnings

- For external use only. Do not apply to broken or irritated skin.
- If skin sensitivity occurs, discontinue use.
- If you have extremely sensitive skin or have had reactions to other adhesives do not use this product.
- Ask a doctor before use: if pregnant or nursing.
- Consult a physician if symptoms persist for more than 7 days or worsen.

- Keep out of the reach of children.

Directions

For best results apply GoPatch immediately when you sense menstrual discomfort or before if you know it will start within an hour. GoPatch can also be applied after menstrual discomfort has begun.

- GoPatch must completely cover the navel. Skin around nevel needs to be clean, dry and free of lotions.
- Remove white backing from one side of GoPatch.
- Smooth over half of navel.
- Remove other half of white backing, smooth remainder over navel.

Remove GoPatch no more than 12 hours after application .

Other information

If you are unsatisfied with GoPatch for any reason, please email us at WeCare@TheGoPatch.com for full money back guarantee.

- Contains no known allergens, free of latex, corn, soy, wheat, and yeast.
- Store at 65-80°F (20-25°C).
- Do not use if tamper seal is broken or missing.

Inactive ingredientsAcrylic adhesive

Questions or comments? Please call us at (707) 244-1945

OTHER SAFETY INFORMATION

* These statements have not been evaluated by the Food and Drug Administration.

Visit us at: www.TheGoPatch.com

Manufactured for: GoPatch, LLC

Healdsburg, CA 95448

GoPatch must COMPLETELY COVER NAVEL

PACKAGE LABEL

GoPatch™

NDC 70105-002-05

Homeopathic

Made in the U.S.A.

Natural Relief Patch for Menstrual Cramps

Drug Free

Latex Free

Up to 12 Hour Relief

5 Patches

PURPOSE

Relieves symptoms of menstrual cramping and discomfort associate with the menstrual period.